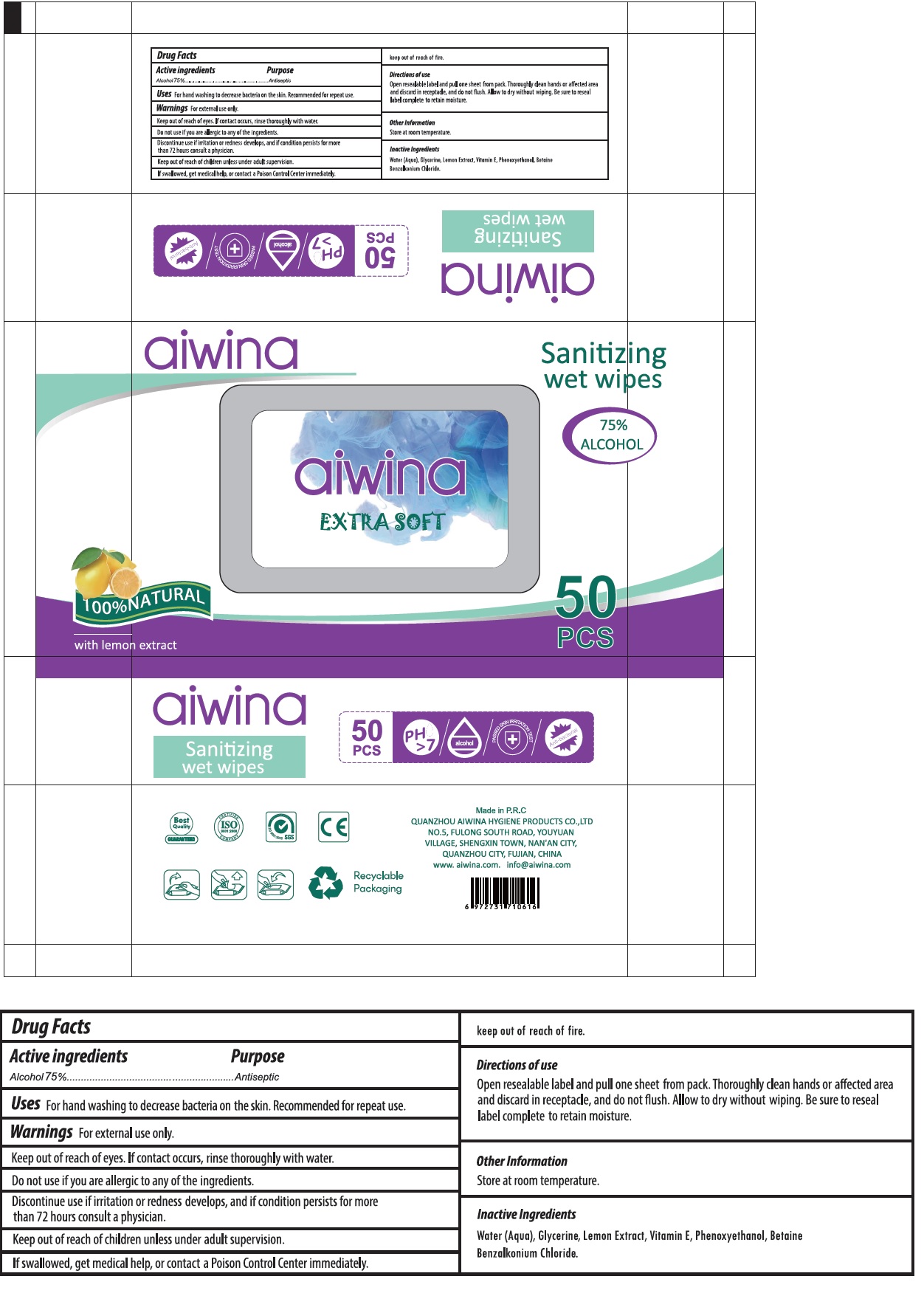 DRUG LABEL: aiwina Sanitizing wet wipes
NDC: 80671-001 | Form: CLOTH
Manufacturer: QUANZHOU AIWINA HYGIENE PRODUCTS CO.,LTD
Category: otc | Type: HUMAN OTC DRUG LABEL
Date: 20200929

ACTIVE INGREDIENTS: ALCOHOL 75 mL/100 mL
INACTIVE INGREDIENTS: WATER; GLYCERIN; LEMON; .ALPHA.-TOCOPHEROL; PHENOXYETHANOL; BETAINE; BENZALKONIUM CHLORIDE

aiwina Sanitizing wet wipes

Active ingredients

Alcohol 75%

Purpose

Antiseptic

INDICATIONS AND USAGE

Uses For hand washing to decrease bacteria on the skin. Recommended for repeat use.

Warnings For external use only.

Keep out of reach of eyes. If contact occurs, rinse thoroughly with water.

Do not use if you are allergic to any of the ingredients.

Discontinue use if irritation or redness develops, and if condition persists for more than 72 hours consult a physician.

Keep out of reach of children unless under adult supervision.

If swallowed, get medical help, or contact a Poison Control Center immediately.

keep out of reach of fire.

Directions of use

Open resealable label and pull one sheet from pack. Thoroughly clean hands or affected area and discard in receptacle, and do not flush. Allow to dry without wiping. Be sure to reseal label complete to retain moisture.

Other Information

Store at room temperature.

Inactive Ingredients

Water (Aqua), Glycerine, Lemon Extract, Vitamin E, Phenoxyethanol, Betaine, Benzalkonium Chloride.

EXTRA SOFT

75% ALCOHOL

100% NATURAL

with lemon extract

PH > 7

alcohol

PASSED SKIN IRRITATION TEST

Anti-bacterial

Best Quality GUARANTEED

ISO 9001:2008 CERTIFIED COMPANY

SYSTEM CERTIFICATION ISO 9001:2000

SGS

Recyclable Packaging

Made in P.R.C

QUANZHOU AIWINA HYGIENE PRODUCTS CO.,LTD

NO.5, FULONG SOUTH ROAD, YOUYUAN VILLAGE, SHENGXIN TOWN, NAN'AN CITY,

QUANZHOU CITY, FUJIAN, CHINA

www.aiwina.com.

info@aiwina.com